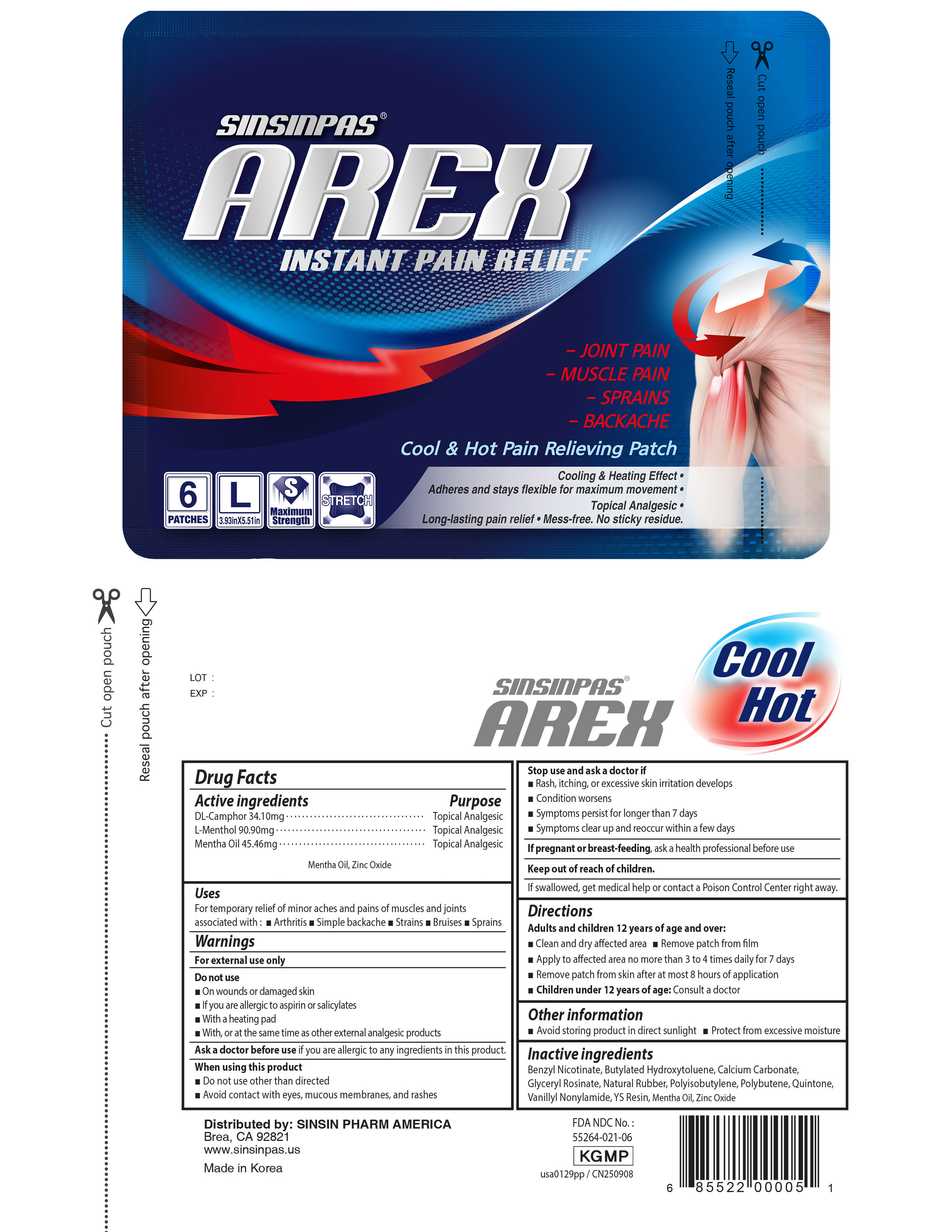 DRUG LABEL: Sinsinpas arex patch large
NDC: 55264-024 | Form: PATCH
Manufacturer: Sinsin Pharmaceutical Co., Ltd.
Category: otc | Type: HUMAN OTC DRUG LABEL
Date: 20260220

ACTIVE INGREDIENTS: METHYL SALICYLATE 90.9 mg/1 1; LEVOMENTHOL 90.9 mg/1 1; CAMPHOR (SYNTHETIC) 34.1 mg/1 1
INACTIVE INGREDIENTS: POLYISOBUTYLENE (200000 MW); ROSIN; POLYBUTENE (1400 MW); GLYCERIN; BENZYL NICOTINAMIDE; BUTYLATED HYDROXYTOLUENE; CALCIUM CARBONATE; NATURAL LATEX RUBBER

SINSINPAS AREX PAIN RELIEVING PATCH, LARGE

ACTIVE INGREDIENT

- DL-Camphor
- L-Menthol
- Methyl Salicylate

PURPOSE

Topical Analgesic

INDICATIONS AND USAGE

For temporary relief of minor aches and pains of muscles and joints associated with:

- arthritis
- simple backache
- strains
- bruises
- sprains

WARNINGS

For external use only

Do not use

- on wounds or damaged skin
- if you are allergic to aspirin or salicylates
- with a heating pad
- with, or at the same time as, other external analgesic products

WARNINGS AND PRECAUTIONS

This product contains natural rubber latex which may cause allergic reactions.

Directions

Adults and children 12 years of age and over:

- Clean and dry affected area
- Remove patch from film
- Apply to affected area not more than 3 to 4 times daily for 7 days.
- Remove patch from skin after at most 8 hours application

Children under 12 years of age:

- Consult a doctor

Other information

- avoid storing product in direct sunlight
- protect from excessive moisture

INACTIVE INGREDIENT

Benzyl Nicothinamide, Butylated Hydroxytoluene, Calcium Carbonate, Glyceryl Rosinate, Natural Rubber, Polyisobutylene, Polybutene, Quintone, Vanillyl Nonylamide, YSResin, Mentha oil, Zinc oxide

SINSIN PHARM. CO., LTD.
Gyeonggi-do, Korea

Keep out of reach of children.